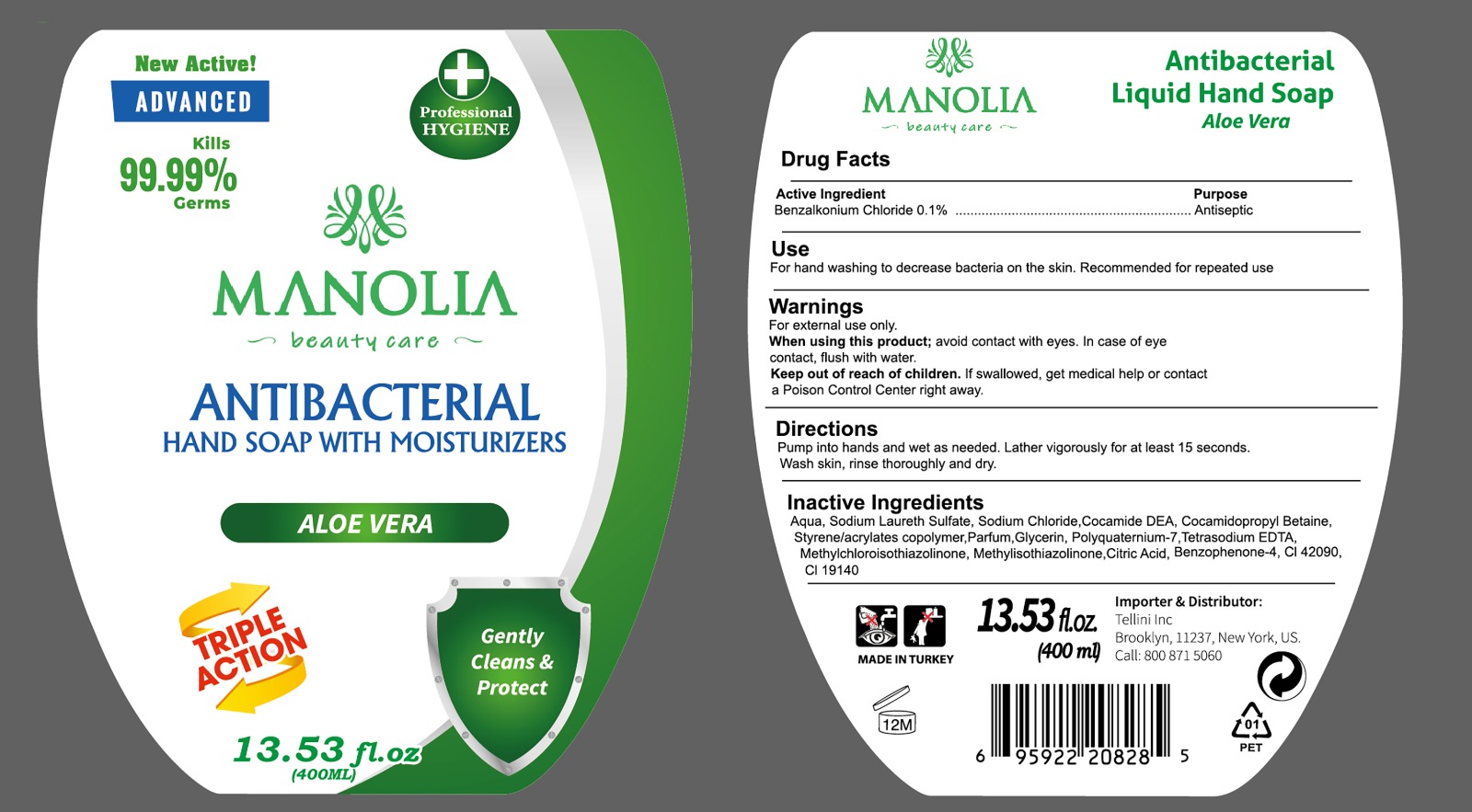 DRUG LABEL: Manolia Antibacterial HandSoap
NDC: 80887-005 | Form: LIQUID
Manufacturer: TELLINI INC.
Category: otc | Type: HUMAN OTC DRUG LABEL
Date: 20201024

ACTIVE INGREDIENTS: BENZALKONIUM CHLORIDE 0.1 g/100 mL
INACTIVE INGREDIENTS: COCAMIDE 1 g/100 mL; GLYCERIN 1 g/100 mL; ETIDRONATE TETRASODIUM 1 g/100 mL; CITRIC ACID ACETATE 1 g/100 mL; POLYQUATERNIUM-7 (70/30 ACRYLAMIDE/DADMAC; 1600 KD) 1 g/100 mL; BENZOPHENONE-5 1 g/100 mL; SODIUM LAURETH SULFATE 1 g/100 mL; COCAMIDOPROPYL BETAINE 1 g/100 mL; WATER; METHYLISOTHIAZOLINONE 1 g/100 mL; METHYLCHLOROISOTHIAZOLINONE 1 g/100 mL; STYRENE/ACRYLAMIDE COPOLYMER (MW 500000) 1 g/100 mL; SODIUM CHLORIDE 1 g/100 mL; CHLORINE 1 g/100 mL

MANOLIA ANTIBACTERIAL HAND SOAP WITH MOISTURIZERS

USE

For hand washing to decrease bacteria on the skin. Recommended for repeated use

WARNINGS

For external use only

When using the product; avoid contact with eyes, In case of eye contact, flush with water.

Keep out reach of children; If swallowed, get medical help or contact a Poison Control Center right away.

DIRECTIONS

Pump into hands and wet as needed. Lather vigorously for at least 15 seconds. Wash skin, rinse thoroughly and dry.

Active Ingredient(s)

Benzalkonium Chloride 0.1% Purpose Antiseptic

Inactive Ingredients

Aqua, Sodium Laureth Sulfate, Sodium Chloride, Cocamide DEA, Cocamidopropyl Betain, Styrene/acrylates copolymer, Parfum, Glycerin, Polyquternium-7, Tetrasodium EDTA, Methylchloroisothiazolinone, Methylisothiazolinone, Citcic Acid, Benzophenone-4, Cl42090, Cl 19140

Keep out of reach of children

If swallowed, get medical help or contact a Poison Control Center right away

Purpose

Antiseptic

Package Label - Principal Display Panel

400 ML Ndc : 80887-005-01